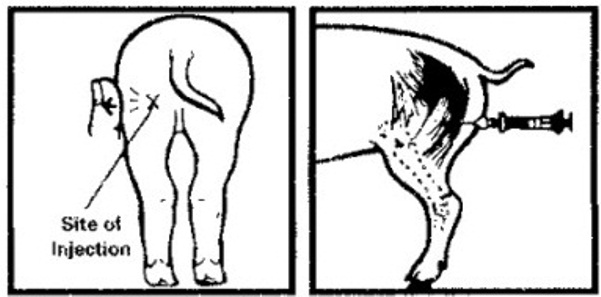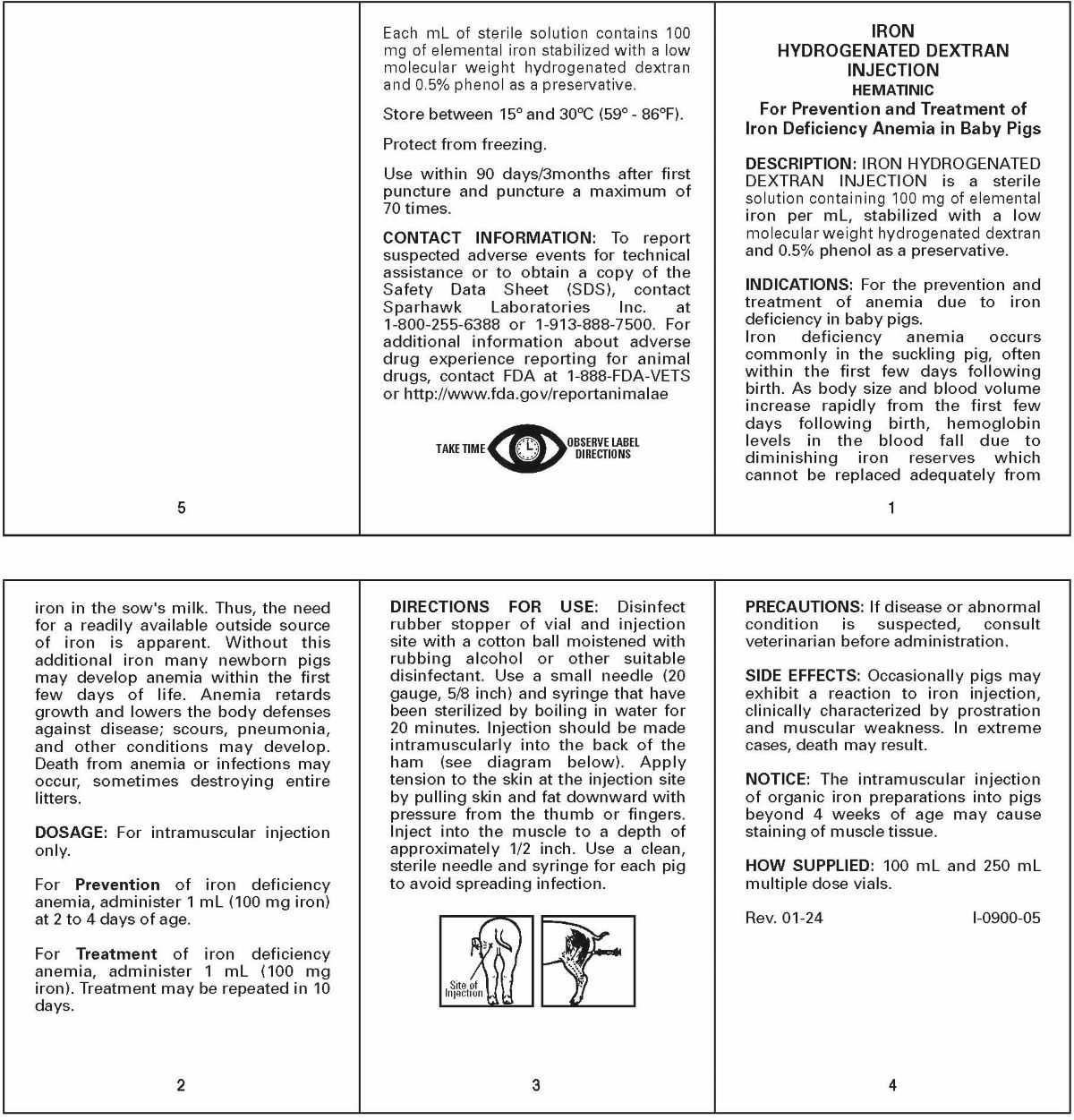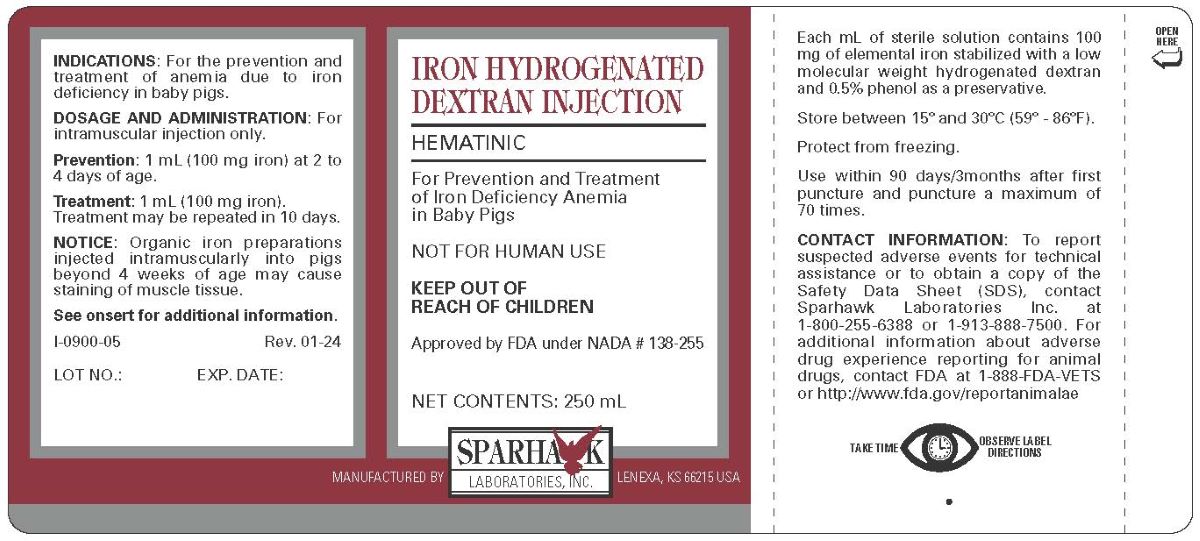 DRUG LABEL: IRON HYDROGENATED DEXTRAN
NDC: 58005-040 | Form: INJECTION
Manufacturer: Sparhawk Laboratories, Inc.
Category: animal | Type: OTC ANIMAL DRUG LABEL
Date: 20240530

ACTIVE INGREDIENTS: IRON 100  mg/1 mL

IRON HYDROGENATED DEXTRAN INJECTION

DESCRIPTION

HEMATINIC

For Prevention and Treatment of Iron Deficiency Anemia in Baby Pigs

NOT FOR HUMAN USE

KEEP OUT OF REACH OF CHILDREN

Approved by FDA under NADA # 138-255

DESCRIPTION

IRON HYDROGENATED DEXTRAN INJECTION is a sterile solution containing 100 mg of elemental iron per mL, stabilized with a low molecular weight hydrogenated dextran and 0.5% phenol as a preservative.

INDICATIONS

For the prevention and treatment of anemia due to iron deficiency in baby pigs.

Iron deficiency anemia occurs commonly in the suckling pig, often within the first few days following birth. As body size and blood volume increase rapidly from the first few days following birth, hemoglobin levels in the blood fall due to diminishing iron reserves which cannot be replaced adequately from iron in the sow's milk. Thus, the need for a readily available outside source of iron is apparent. Without this additional iron many newborn pigs may develop anemia within the first few days of life. Anemia retards growth and lowers the body defenses against disease; scours, pneumonia, and other conditions may develop. Death from anemia or infections may occur, sometimes destroying entire litters.

DOSAGE

For intramuscular injection only.

For Prevention of iron deficiency anemia, administer 1 mL (100 mg iron) at 2 to 4 days of age.

For Treatment of iron deficiency anemia, administer 1 mL (100 mg iron). Treatment may be repeated in 10 days.

DIRECTIONS FOR USE

Disinfect rubber stopper of vial and injection site with a cotton ball moistened with rubbing alcohol or other suitable disinfectant. Use a small needle (20 gauge, 5/8 inch) and syringe that have been sterilized by boiling in water for 20 minutes. Injection should be made intramuscularly into the back of the ham (see diagram below). Apply tension to the skin at the injection site by pulling skin and fat downward with pressure from the thumb or fingers. Inject into the muscle to a depth of approximately 1/2 inch. Use a clean, sterile needle and syringe for each pig to avoid spreading infection.

PRECAUTIONS

If disease or abnormal condition is suspected, consult veterinarian before administration.

SIDE EFFECTS

Occasionally pigs may exhibit a reaction to iron injection, clinically characterized by prostration and muscular weakness. In extreme cases, death may result.

NOTICE: The intramuscular injection of organic iron preparations into pigs beyond 4 weeks of age may cause staining of muscle tissue.

HOW SUPPLIED

100 mL multiple dose vials.

STORAGE AND HANDLING

Store at controlled room temperature between 15o and 30oC (59o - 86oF).

Protect from freezing.

TAKE TIME OBSERVE LABEL DIRECTIONS

Use within 90 days/3months after first
puncture and puncture a maximum of
70 times.

CONTACT INFORMATION

To report suspected adverse events for technical
assistance or to obtain a copy of the
Safety Data Sheet (SDS), contact
Sparhawk Laboratories Inc. at
1-800-255-6388 or 1-913-888-7500. For
additional information about adverse
drug experience reporting for animal
drugs, contact FDA at 1-888-FDA-VETS
or http://www.fda.gov/reportanimalae